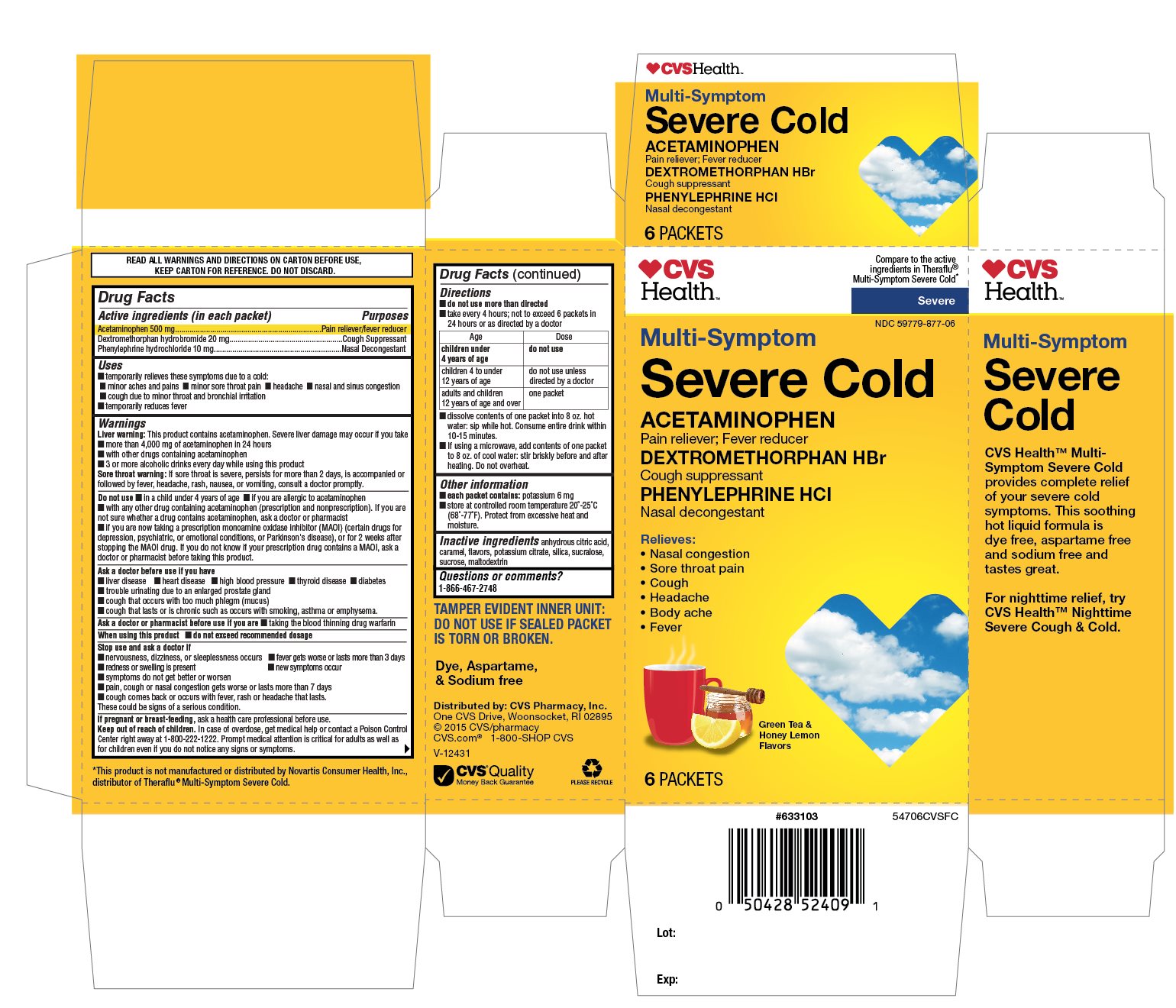 DRUG LABEL: CVS Health Multi Symptom Severe Cold
NDC: 59779-877 | Form: POWDER, FOR SOLUTION
Manufacturer: CVS Pharmacy,Inc.
Category: otc | Type: HUMAN OTC DRUG LABEL
Date: 20190724

ACTIVE INGREDIENTS: ACETAMINOPHEN 500 mg/1 1; DEXTROMETHORPHAN HYDROBROMIDE 20 mg/1 1; PHENYLEPHRINE HYDROCHLORIDE 10 mg/1 1
INACTIVE INGREDIENTS: ANHYDROUS CITRIC ACID; CARAMEL; MALTODEXTRIN; POTASSIUM CITRATE; SILICON DIOXIDE; SUCRALOSE; SUCROSE

CVS Health Multi-Symptom Severe Cold Green Tea and Honey Lemon Flavors 6 Packets

Active ingredients (in each packet)

Acetaminophen 500 mg

Dextromethorphan hydrobromide 20 mg

Phenylephrine hydrochloride 10 mg

Purposes

Pain reliever / fever reducer

Cough Suppressant

Nasal Decongestant

Uses

- temporarily relieves these symptoms due to a cold:
• minor aches and pains
• minor sore throat pain
• headache
• nasal and sinus congestion
• cough due to minor throat and bronchial irritation
- temporarily reduces fever

Warnings

Liver warning: This product contains acetaminophen. Severe liver damage may occur if you take

- more than 4,000 mg of acetaminophen in 24 hours
- with other drugs containing acetaminophen
- 3 or more alcoholic drinks every day while using this product

Sore throat warning: If sore throat is severe, persists for more than 2 days, is accompanied or followed by fever, headache, rash, nausea, or vomiting consult a doctor promptly.

Do not use

- in a child under 4 years of age
- if you are allergic to acetaminophen
- with any other drug containing acetaminophen (prescription or nonprescription). If you are not sure whether a drug contains acetaminophen, ask a doctor or a pharmacist.
- if you are now taking a prescription monoamine oxidase inhibitor (MAOI) (certain drugs for depression, psychiatric, or emotional conditions, or Parkinson's disease), or for 2 weeks after stopping the MAOI drug. If you do not know if your prescription drug contains a MAOI, ask a doctor or pharmacist before taking this product.

Ask a doctor before use if you have

- liver disease
- heart disease
- high blood pressure
- thyroid disease
- diabetes
- trouble urinating due to an enlarged prostate gland
- cough that occurs with too much phlegm (mucus)
- cough that lasts or is chronic such as occurs with smoking, asthma or emphysema

Ask a doctor or pharmacist before use if you are

taking the blood thinning drug warfarin

When using this product

do not exceed recommended dosage

Stop use and ask a doctor if

- nervousness, dizziness, or sleeplessness occurs
- fever gets worse or lasts more than 3 days
- redness or swelling is present
- new symptoms occur
- symptoms do not get better or worsen
- pain, cough or nasal congestion gets worse or lasts more than 7 days
- cough comes back or occurs with fever, rash or headache that lasts. These could be signs of a serious condition.

If pregnant or breast-feeding,

ask a health care professional before use.

Keep out of reach of children.

In case of overdose, get medical help or contact a Poison Control Center right away at 1-800-222-1222. Prompt medical attention is critical for adults as well as for children even if you do not notice any signs or symptoms.

Directions

- do not use more than directed
- take every 4 hours ; not to exceed 6 packets in 24 hours or as directed by a doctor

Age | Dose
children under 4 years of age | do not use
children 4 to under 12 years of age | do not use unless directed by a doctor
adults and children 12 years of age and over | one packet

- dissolve contents of one packet into 8 oz. hot water: sip while hot. Consume entire drink within 10 - 15 minutes.
- if using a microwave, add contents of one packet to 8 oz. of cool water: stir briskly before and after heating, Do not overheat.

Other information

- each packet contains: potassium 6 mg
- store at controlled room temperature 20°-25°C (68°-77°F). Protect from excessive heat and moisture.

Inactive ingredients

anhydrous citric acid, caramel, flavors, maltodextrin ,potassium citrate, silica, sucralose, sucrose,

Questions or Comments

1-866-467-2748

Principal Display

CVS Health™

Compare to the active ingredients in Theraflu® Multi-Symptom Severe Cold*

Severe

NDC 59779-877-06

Multi-Symptom

Severe Cold

ACETAMINOPHEN

Pain reliever; Fever reducer

DEXTROMETHORPHAN HBr

Cough suppressant

PHENYLEPHRINE HCl

Nasal decongestant

Relieves:

- Nasal congestion
- Sore throat pain
- Cough
- Headache
- Body ache
- Fever

Green Tea & Honey Lemon Flavors

6 PACKETS

READ ALL WARNINGS AND DIRECTIONS ON CARTON BEFORE USE, KEEP CARTON FOR REFERENCE, DO NOT DISCARD,

Multi-Symptom Severe Cold

CVS Health™ Multi-Symptom Severe Cold provides complete relief of your severe cold symptoms. This soothing hot liquid formula is dye free, aspartame free and sodium free and tastes great.

For nighttime relief, try CVS Health™ Nighttime Severe Cough & Cold.

TAMPER EVIDENT INNER UNIT: DO NOT USE IF SEALED PACKET IS TORN OR BROKEN.

Dye, Aspartame, & Sodium free

Distributed by: CVS Pharmacy, Inc.

One CVS Drive, Woonsocket, RI 02895

©2015 CVS/pharmacy

CVS.com® 1-800-SHOP CVS

V-12431

CVS® Quality

Money back Guarantee

*This product is not manufactured or distributed by Novartis Consumer Health Inc., distributor of Theraflu® Multi-Symptom Severe Cold